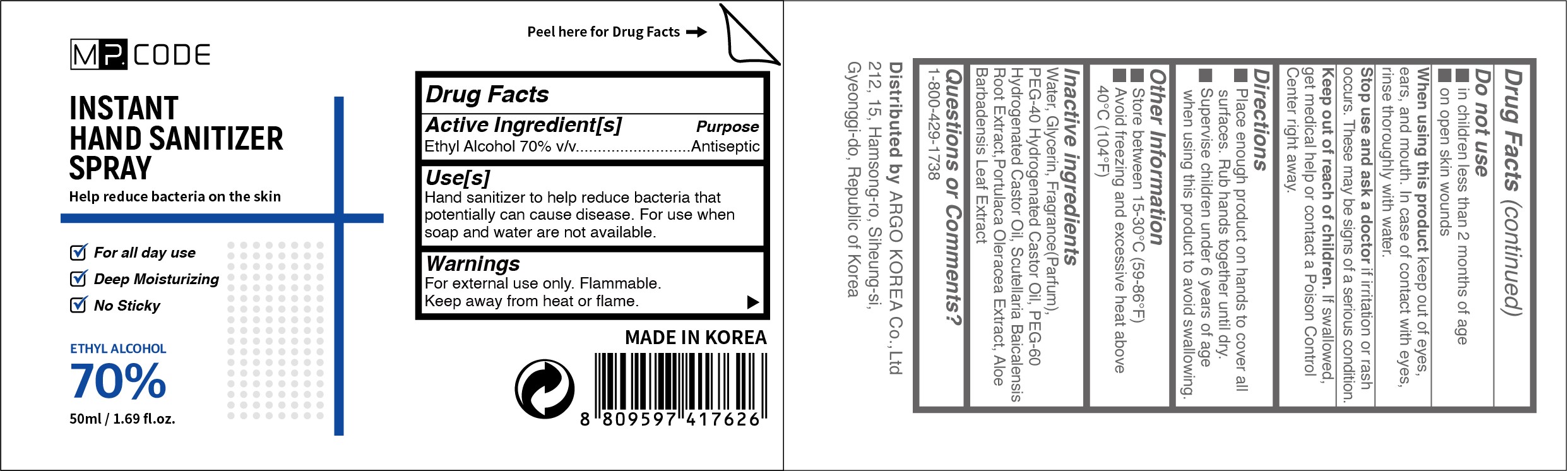 DRUG LABEL: MP. CODE INSTANT HAND SANITIZER 70% 50ml
NDC: 76887-105 | Form: SPRAY
Manufacturer: ARGO KOREA Co., Ltd
Category: otc | Type: HUMAN OTC DRUG LABEL
Date: 20201020

ACTIVE INGREDIENTS: ALCOHOL 70 mL/100 mL
INACTIVE INGREDIENTS: POLYOXYL 40 HYDROGENATED CASTOR OIL; PURSLANE; ALOE VERA LEAF; GLYCERIN; SCUTELLARIA BAICALENSIS ROOT; WATER; PEG-60 HYDROGENATED CASTOR OIL

MP. CODE INSTANT HAND SANITIZER SPRAY 50ml

Active Ingredient(s)

Ethyl Alcohol 70% v/v. Purpose: Antiseptic

Purpose

Antiseptic, Hand Sanitizer

Use

Hand Sanitizer to help reduce bacteria that potentially can cause disease. For use when soap and water are not available.

Warnings

For external use only. Flammable. Keep away from heat or flame

Do not use

- in children less than 2 months of age
- on open skin wounds

When using this product keep out of eyes, ears, and mouth. In case of contact with eyes, rinse eyes thoroughly with water.

Stop use and ask a doctor if irritation or rash occurs. These may be signs of a serious condition.

Keep out of reach of children. If swallowed, get medical help or contact a Poison Control Center right away.

Directions

- Place enough product on hands to cover all surfaces. Rub hands together until dry.
- Supervise children under 6 years of age when using this product to avoid swallowing.

Other information

- Store between 15-30C (59-86F)
- Avoid freezing and excessive heat above 40C (104F)

Inactive ingredients

Water, Glycerin, Fragrance(Parfum), PEG-40 Hydrogenated Castor Oil, PEG-60 Hydrogenated Castor Oil, Scutellaria Baicalensis Root Extract, Portulaca Oleracea Extract, Aloe Barbadensis Leaf Extract

Package Label - Principal Display Panel

MP. CODE
INSTANT
HAND SANITIZER
SPRAY
Help reduce bacteria on the skin
- For all day use
- Deep Moisturizing
- No Sticky
ETHYL ALCOHOL
70%
50ml / 1.69fl.oz.